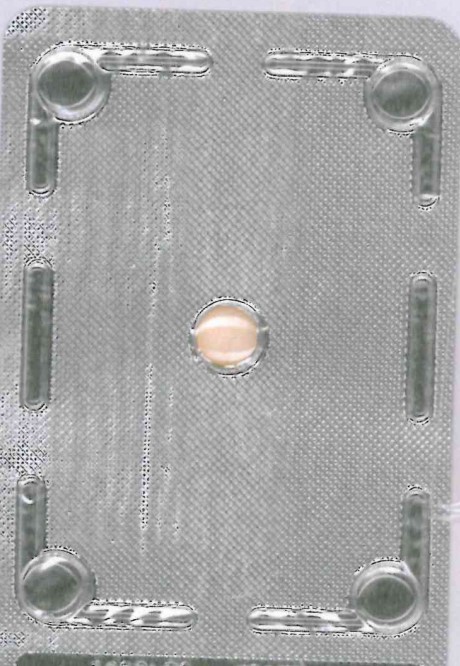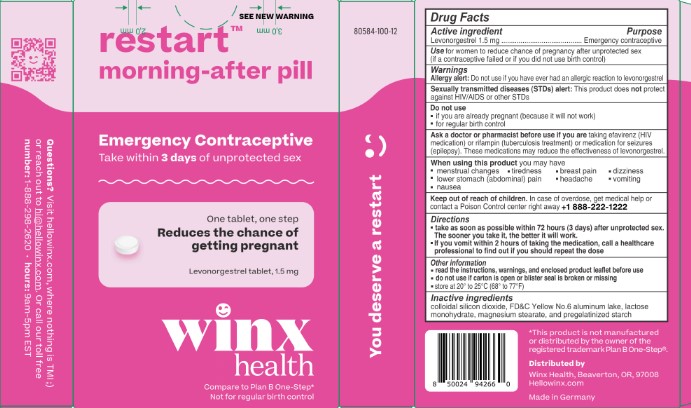 DRUG LABEL: Restart
NDC: 80584-103 | Form: TABLET
Manufacturer: Winx Health Inc.
Category: otc | Type: HUMAN OTC DRUG LABEL
Date: 20250827

ACTIVE INGREDIENTS: LEVONORGESTREL 1.5 mg/1 1
INACTIVE INGREDIENTS: MAGNESIUM STEARATE; FD&C YELLOW NO. 6; TALC; LACTOSE MONOHYDRATE; SILICON DIOXIDE; STARCH, CORN

PACKAGE LABEL

DOSAGE AND ADMINISTRATION

- Take as soon as possible within 72 hours (3 days) after unprotected sex. The sooner you take it the better it will work.
- If you vomit within 2 hours after taking the medication, call a healthcare professional to find out if you should repeat the dose

Allergy Alert: Do not use if you have ever had an allergic reaction to levonorgestrel

Sexually transmitted diseases (STDs) alert: This product does not protect against HIV/AIDS or other STDs

Do not use

- If you are already pregnant (because it will not work)
- For regular birth control

Ask a doctor or pharmacist before use if you are

- Taking efavirenz (HIV medication) or rifampin (tuberculosis treatment) or medication for seizures (epilepsy). These medications may reduce the effectiveness of levonorgestrel.

When using this product you may have

- Menstrual changes
- Tiredness
- Breast pain
- Nausea
- Headache
- Vomiting
- Lower stomach (abdominal) pain
- Dizziness

Keep out of reach of children.

In case of overdose, get medical help or contact a Poison Control Center right away (1-800-222-1222).

INACTIVE INGREDIENT

Colloidal Silicon Dioxide, Corn Starch, Lactose Monohydrate, Magnesium Dtearate, Povidone

INDICATIONS AND USAGE

For women to reduce chance of pregnancy after unprotected sex (if a contraceptive failed or if you did not use birth control)

Keep out of reach of children.

In case of overdose, get medical help or contact a Poison Control Center right away (1-800-222-1222).

PURPOSE

Emergency Contraceptive

ACTIVE INGREDIENT

Levonorgestrel 1.5 mg